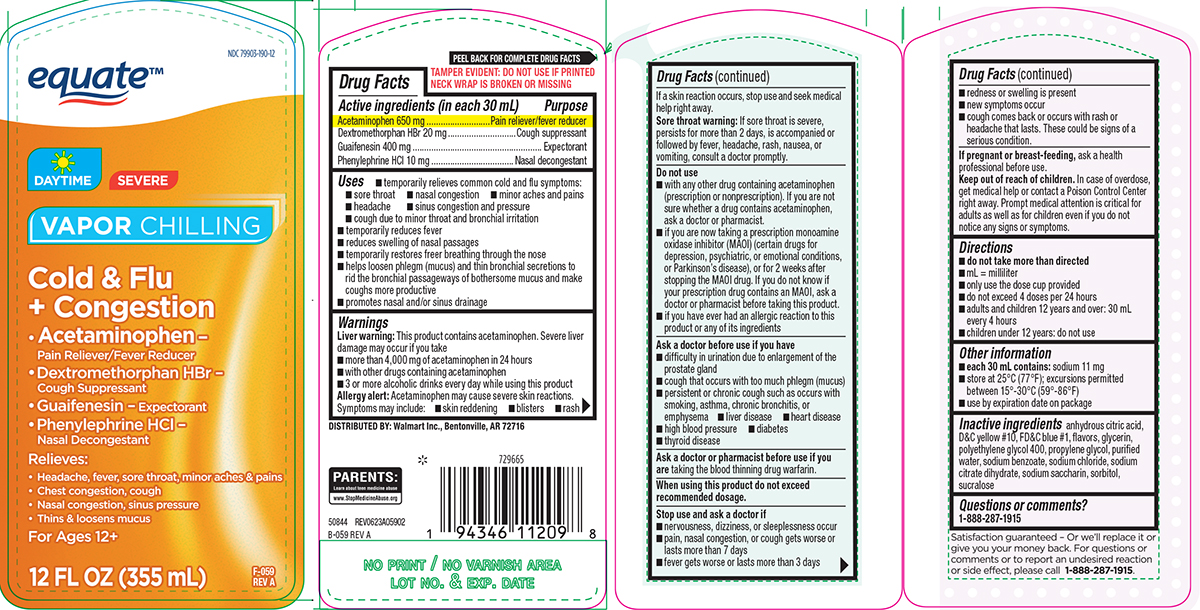 DRUG LABEL: Cold and Flu plus Congestion
NDC: 79903-190 | Form: SOLUTION
Manufacturer: WALMART INC.
Category: otc | Type: HUMAN OTC DRUG LABEL
Date: 20260204

ACTIVE INGREDIENTS: ACETAMINOPHEN 650 mg/30 mL; DEXTROMETHORPHAN HYDROBROMIDE 20 mg/30 mL; GUAIFENESIN 400 mg/30 mL; PHENYLEPHRINE HYDROCHLORIDE 10 mg/30 mL
INACTIVE INGREDIENTS: ANHYDROUS CITRIC ACID; D&C YELLOW NO. 10; FD&C BLUE NO. 1; GLYCERIN; POLYETHYLENE GLYCOL 400; PROPYLENE GLYCOL; WATER; SODIUM BENZOATE; SODIUM CHLORIDE; TRISODIUM CITRATE DIHYDRATE; SACCHARIN SODIUM; SORBITOL; SUCRALOSE

Equate 44-059

Active ingredients (in each 30 mL)

Acetaminophen 650 mg
Dextromethorphan HBr 20 mg
Guaifenesin 400 mg
Phenylephrine HCl 10 mg

Purpose

Pain reliever/fever reducer
Cough suppressant
Expectorant
Nasal decongestant

Uses

- temporarily relieves common cold and flu symptoms:
  - sore throat
  - nasal congestion
  - minor aches and pains
  - headache
  - sinus congestion and pressure
  - cough due to minor throat and bronchial irritation
- temporarily reduces fever
- reduces swelling of nasal passages
- temporarily restores freer breathing through the nose
- helps loosen phlegm (mucus) and thin bronchial secretions to rid the bronchial passageways of bothersome mucus and make coughs more productive
- promotes nasal and/or sinus drainage

Warnings

Liver warning: This product contains acetaminophen. Severe liver damage may occur if you take

- more than 4,000 mg of acetaminophen in 24 hours
- with other drugs containing acetaminophen
- 3 or more alcoholic drinks every day while using this product

Allergy alert: Acetaminophen may cause severe skin reactions. Symptoms may include:

- skin reddening
- blisters
- rash

If a skin reaction occurs, stop use and seek medical help right away.

Sore throat warning: If sore throat is severe, persists for more than 2 days, is accompanied or followed by fever, headache, rash, nausea, or vomiting, consult a doctor promptly.

Do not use

- with any other drug containing acetaminophen (prescription or nonprescription). If you are not sure whether a drug contains acetaminophen, ask a doctor or pharmacist.
- if you are now taking a prescription monoamine oxidase inhibitor (MAOI) (certain drugs for depression, psychiatric, or emotional conditions, or Parkinson’s disease), or for 2 weeks after stopping the MAOI drug. If you do not know if your prescription drug contains an MAOI, ask a doctor or pharmacist before taking this product.
- if you have ever had an allergic reaction to this product or any of its ingredients

Ask a doctor before use if you have

- difficulty in urination due to enlargement of the prostate gland
- cough that occurs with too much phlegm (mucus)
- persistent or chronic cough such as occurs with smoking, asthma, chronic bronchitis, or emphysema
- liver disease
- heart disease
- high blood pressure
- diabetes
- thyroid disease

Ask a doctor or pharmacist before use if you are

taking the blood thinning drug warfarin.

When using this product

do not exceed recommended dosage.

Stop use and ask a doctor if

- nervousness, dizziness, or sleeplessness occur
- pain, nasal congestion, or cough gets worse or lasts more than 7 days
- fever gets worse or lasts more than 3 days
- redness or swelling is present
- new symptoms occur
- cough comes back or occurs with rash or headache that lasts. These could be signs of a serious condition.

If pregnant or breast-feeding,

ask a health professional before use.

Keep out of reach of children.

In case of overdose, get medical help or contact a Poison Control Center right away. Prompt medical attention is critical for adults as well as for children even if you do not notice any signs or symptoms.

Directions

- do not take more than directed
- mL = milliliter
- only use the dose cup provided
- do not exceed 4 doses per 24 hours
- adults and children 12 years and over: 30 mL every 4 hours
- children under 12 years: do not use

Other information

- each 30 mL contains: sodium 11 mg
- store at 25°C (77°F); excursions permitted between 15°-30°C (59°-86°F)
- use by expiration date on package

Inactive ingredients

anhydrous citric acid, D&C yellow #10, FD&C blue #1, flavors, glycerin, polyethylene glycol 400, propylene glycol, purified water, sodium benzoate, sodium chloride, sodium citrate dihydrate, sodium saccharin, sorbitol, sucralose

Questions or comments?

1-888-287-1915

Principal display panel

equate™

NDC 79903-190-12

DAYTIME
SEVERE
VAPOR CHILLING

Cold & Flu
+ Congestion

• Acetaminophen -
Pain Reliever/Fever Reducer

• Dextromethorphan HBr -
Cough Suppressant

• Guaifenesin - Expectorant

• Phenylephrine HCl -
Nasal Decongestant

Relieves:

• Headache, fever, sore throat, minor aches & pains
• Chest congestion, cough
• Nasal congestion, sinus pressure
• Thins & loosens mucus

For Ages 12+

12 FL OZ (355 mL)

F-059
REV A

DISTRIBUTED BY: Walmart Inc., Bentonville, AR 72716

PARENTS:
Learn about teen medicine abuse
www.StopMedicineAbuse.org

50844 REV0623A05902
B-059 REV A

Satisfaction guaranteed - Or we'll replace it or
give you your money back. For questions or
comments or to report an undesired reaction
or side effect, please call 1-888-287-1915.

Equate 44-059